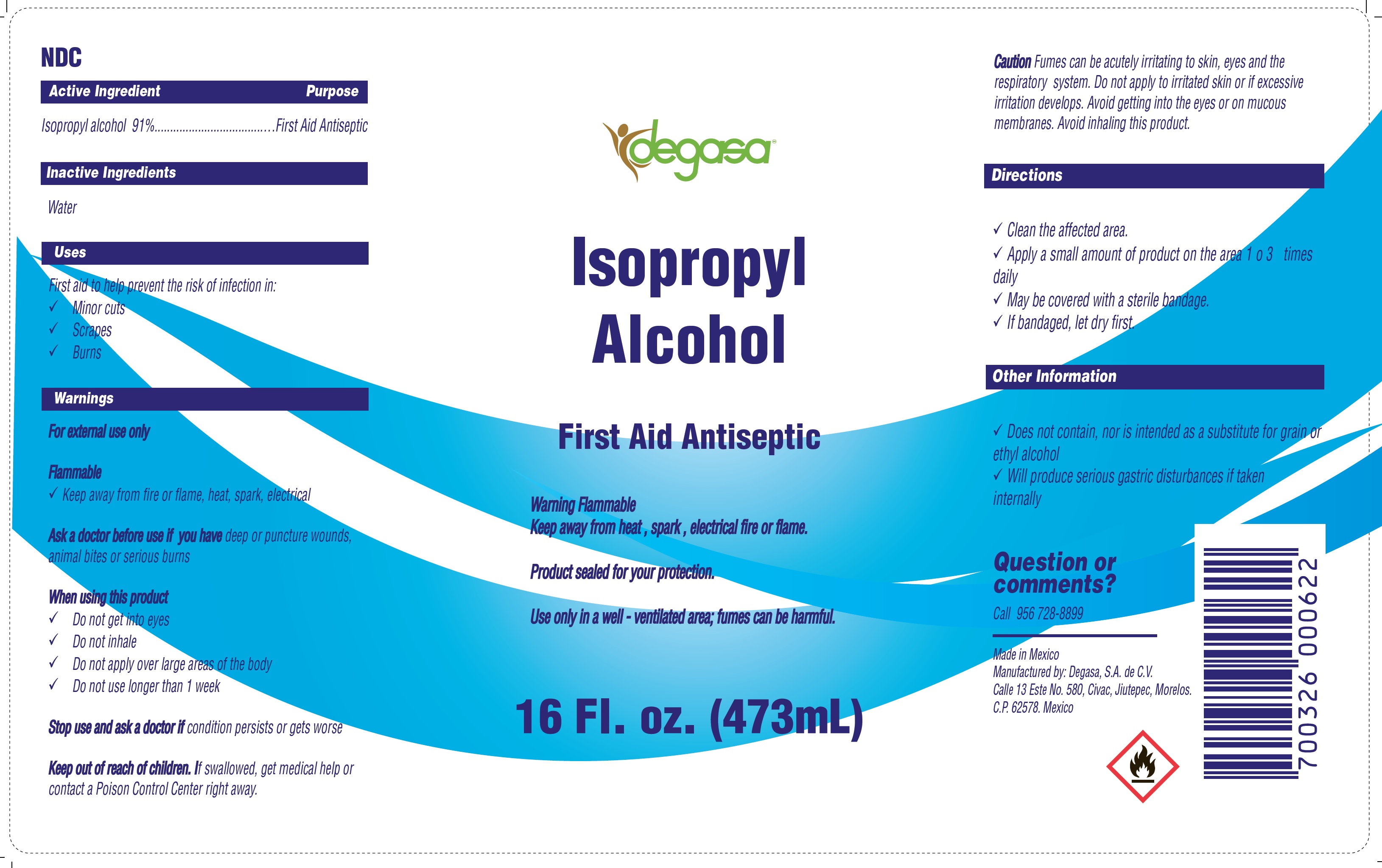 DRUG LABEL: ISOPROPYL ALCOHOL
NDC: 67326-035 | Form: LIQUID
Manufacturer: Degasa, S.A. de C.V.
Category: otc | Type: HUMAN OTC DRUG LABEL
Date: 20231105

ACTIVE INGREDIENTS: ISOPROPYL ALCOHOL 0.91 mL/1 mL
INACTIVE INGREDIENTS: WATER

ISOPROPYL ALCOHOL 91%

Active Ingredient

Isopropyl alcohol 91%

Purpose

First Aid Antiseptic

Inactive Ingredients

Water

Uses

First aid to help prevent the risk of infection in:

- Minor cuts
- Scrapes
- Burns

Warnings

For external use only Flammable

- Keep away from fire or flame, heat, spark, electrical

Ask a doctor before use if you have

deep or puncture wounds, animal bites or serious burns

When using this product

- Do not get into eyes
- Do not inhale
- Do not apply over large areas of the body
- Do not use longer than 1 week

Stop use and ask a doctor if

condition persists or gets worse

Keep out of reach of children.

If swallowed, get medical help or contact a Poison Control Center right away.

Caution

Fumes can be acutely irritating to skin, eyes and the respiratory system. Do not apply to irritated skin or if excessive irritation develops. Avoid getting into the eyes or on mucous membranes. Avoid inhaling this product.

Directions

- Clean the affected area.
- Apply a small amount of product on the area 1 o 3 times daily
- May be covered with a sterile bandage.
- If bandaged, let dry first.

Other Information

- Does not contain, nor is intended as a substitute for grain or ethyl alcohol
- Will produce serious gastric disturbances if taken internally

Question or comments?

Call 956 728-8899